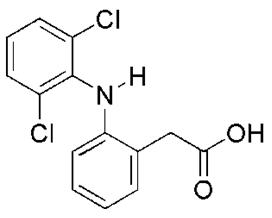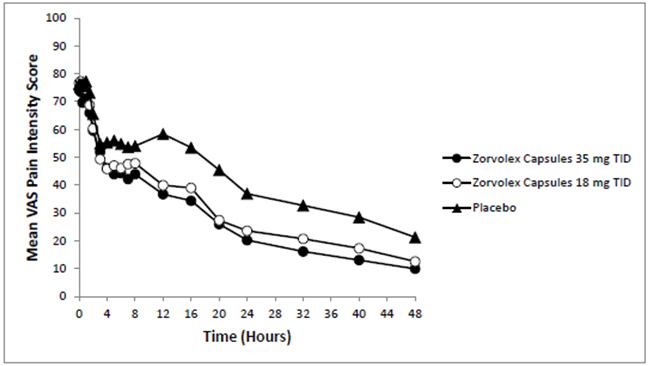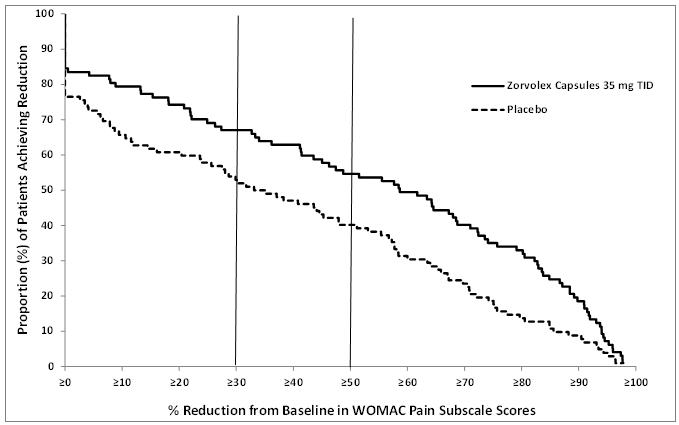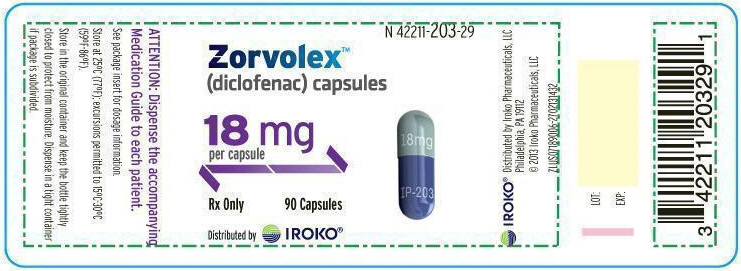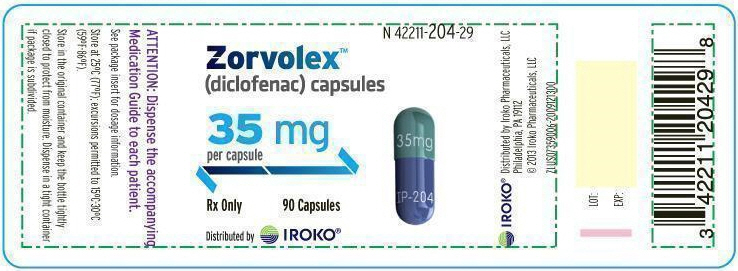 DRUG LABEL: Zorvolex
NDC: 42211-203 | Form: CAPSULE
Manufacturer: Iroko Pharmaceuticals LLC
Category: prescription | Type: HUMAN PRESCRIPTION DRUG LABEL
Date: 20190408

ACTIVE INGREDIENTS: DICLOFENAC 18 mg/1 1
INACTIVE INGREDIENTS: LACTOSE MONOHYDRATE; SODIUM LAURYL SULFATE; CELLULOSE, MICROCRYSTALLINE; CROSCARMELLOSE SODIUM; SODIUM STEARYL FUMARATE; GELATIN; TITANIUM DIOXIDE; FD&C BLUE NO. 1; FD&C BLUE NO. 2; FERRIC OXIDE YELLOW; FERROSOFERRIC OXIDE

HIGHLIGHTS OF PRESCRIBING INFORMATION

These highlights do not include all the information needed to use ZORVOLEX® safely and effectively. See full prescribing information for ZORVOLEX.
ZORVOLEX (diclofenac) capsules, for oral use
Initial U.S. Approval: 1988

WARNING: RISK OF SERIOUS CARDIOVASCULAR AND GASTROINTESTINAL EVENTS

See full prescribing information for complete boxed warning.

- Nonsteroidal anti-inflammatory drugs (NSAIDs) cause an increased risk of serious cardiovascular thrombotic events, including myocardial infarction and stroke, which can be fatal. This risk may occur early in treatment and may increase with duration of use (5.1)
- ZORVOLEX is contraindicated in the setting of coronary artery bypass graft (CABG) surgery (4, 5.1)
- NSAIDs cause an increased risk of serious gastrointestinal (GI) adverse events including bleeding, ulceration, and perforation of the stomach or intestines, which can be fatal. These events can occur at any time during use and without warning symptoms. Elderly patients and patients with a prior history of peptic ulcer disease and/or GI bleeding are at greater risk for serious GI events (5.2)

RECENT MAJOR CHANGES

Boxed Warning | 5/2016
Warnings and Precautions, Cardiovascular Thrombotic Events (5.1) | 5/2016
Warnings and Precautions, Heart Failure and Edema (5.5) | 5/2016

1 INDICATIONS AND USAGE

ZORVOLEX is a nonsteroidal anti-inflammatory drug indicated for

- management of mild to moderate acute pain (1)
- management of osteoarthritis pain.(1)

2 DOSAGE AND ADMINISTRATION

- Use the lowest effective dosage for shortest duration consistent with individual patient treatment goals. (2)
- The dosage for acute pain is 18 mg or 35 mg orally three times a day. (2)
- The dosage for osteoarthritis pain is 35 mg orally three times a day. (2)

3 DOSAGE FORMS AND STRENGTHS

ZORVOLEX (diclofenac) capsules: 18 mg and 35 mg (3)

4 CONTRAINDICATIONS

- Known hypersensitivity to diclofenac or any components of the drug product (4)
- History of asthma, urticaria, or other allergic-type reactions after taking aspirin or other NSAIDs (4)
- In the setting of CABG surgery (4)

5 WARNINGS AND PRECAUTIONS

- Hepatotoxicity: Inform patients of warning signs and symptoms of hepatotoxicity. Discontinue if abnormal liver tests persist or worsen or if clinical signs and symptoms of liver disease develop (5.3)
- Hypertension: Patients taking some antihypertensive medications may have impaired response to these therapies when taking NSAIDs. Monitor blood pressure (5.4, 7)
- Heart Failure and Edema: Avoid use of ZORVOLEX in patients with severe heart failure unless benefits are expected to outweigh risk of worsening heart failure (5.5)
- Renal Toxicity: Monitor renal function in patients with renal or hepatic impairment, heart failure, dehydration, or hypovolemia. Avoid use of ZORVOLEX in patients with advanced renal disease unless benefits are expected to outweigh risk of worsening renal function (5.6)
- Anaphylactic Reactions: Seek emergency help if an anaphylactic reaction occurs (5.7)
- Exacerbation of Asthma Related to Aspirin Sensitivity: ZORVOLEX is contraindicated in patients with aspirin-sensitive asthma. Monitor patients with preexisting asthma (without aspirin sensitivity) (5.8)
- Serious Skin Reactions: Discontinue ZORVOLEX at first appearance of skin rash or other signs of hypersensitivity (5.9)
- Premature Closure of Fetal Ductus Arteriosus: Avoid use in pregnant women starting at 30 weeks gestation (5.10, 8.1)
- Hematologic Toxicity: Monitor hemoglobin or hematocrit in patients with any signs or symptoms of anemia (5.11, 7)

6 ADVERSE REACTIONS

Most common adverse reactions (incidence ≥2%) are edema, nausea, headache, dizziness, vomiting, constipation, pruritus, diarrhea, flatulence, pain in extremity, abdominal pain, sinusitis, alanine aminotransferase increased, blood creatinine increased, hypertension, and dyspepsia. (6.1)

To report SUSPECTED ADVERSE REACTIONS, contact Iroko Pharmaceuticals, LLC at 1-877-757-0676 or FDA at 1-800-FDA-1088 or www.fda.gov/medwatch.

7 DRUG INTERACTIONS

- Drugs that Interfere with Hemostasis (e.g. warfarin, aspirin, SSRIs/SNRIs): Monitor patients for bleeding who are concomitantly taking ZORVOLEX with drugs that interfere with hemostasis. Concomitant use of ZORVOLEX and analgesic doses of aspirin is not generally recommended (7)
- ACE Inhibitors, Angiotensin Receptor Blockers (ARB), or Beta-Blockers: Concomitant use with ZORVOLEX may diminish the antihypertensive effect of these drugs. Monitor blood pressure (7)
- ACE Inhibitors and ARBs: Concomitant use with ZORVOLEX in elderly, volume depleted, or those with renal impairment may result in deterioration of renal function. In such high risk patients, monitor for signs of worsening renal function (7)
- Diuretics: NSAIDs can reduce natriuretic effect of furosemide and thiazide diuretics. Monitor patients to assure diuretic efficacy including antihypertensive effects (7)
- Digoxin: Concomitant use with ZORVOLEX can increase serum concentration and prolong half-life of digoxin. Monitor serum digoxin levels (7)

8 USE IN SPECIFIC POPULATIONS

Pregnancy: Use of NSAIDs during the third trimester of pregnancy increases the risk of premature closure of the fetal ductus arteriosus. Avoid use of NSAIDs in pregnant women starting at 30 weeks gestation (5.10, 8.1)

Infertility: NSAIDs are associated with reversible infertility. Consider withdrawal of ZORVOLEX in women who have difficulties conceiving (8.3)

FULL PRESCRIBING INFORMATION

WARNING: RISK OF SERIOUS CARDIOVASCULAR AND GASTROINTESTINAL EVENTS

Cardiovascular Thrombotic Events

- Nonsteroidal anti-inflammatory drugs (NSAIDs) cause an increased risk of serious cardiovascular thrombotic events, including myocardial infarction and stroke, which can be fatal. This risk may occur early in treatment and may increase with duration of use [see Warnings and Precautions (5.1)].
- ZORVOLEX is contraindicated in the setting of coronary artery bypass graft (CABG) surgery [see Contraindications (4) and Warnings and Precautions (5.1)].

Gastrointestinal Bleeding, Ulceration, and Perforation

- NSAIDs cause an increased risk of serious gastrointestinal (GI) adverse events including bleeding, ulceration, and perforation of the stomach or intestines, which can be fatal. These events can occur at any time during use and without warning symptoms. Elderly patients and patients with a prior history of peptic ulcer disease and/or GI bleeding are at greater risk for serious GI events [see Warnings and Precautions (5.2)].

1 INDICATIONS AND USAGE

ZORVOLEX is indicated for:

- Management of mild to moderate acute pain
- Management of osteoarthritis pain

2 DOSAGE AND ADMINISTRATION

2.1 General Dosing Instructions

Carefully consider the potential benefits and risks of ZORVOLEX and other treatment options before deciding to use ZORVOLEX. Use the lowest effective dosage for the shortest duration consistent with individual patient treatment goals [see Warnings and Precautions (5)].

The effectiveness of ZORVOLEX when taken with food has not been studied in clinical studies. Taking ZORVOLEX with food may cause a reduction in effectiveness compared to taking ZORVOLEX on an empty stomach [see Clinical Pharmacology (12)].

Acute Pain

For management of mild to moderate acute pain, the dosage is 18 mg or 35 mg orally three times daily.

Osteoarthritis Pain

For management of osteoarthritis pain, the dosage is 35 mg orally three times daily.

2.2 Dosage Adjustments in Patients with Hepatic Impairment

Patients with hepatic disease may require reduced doses of ZORVOLEX compared to patients with normal hepatic function [see Clinical Pharmacology (12)]. As with other diclofenac products, start treatment at the lowest dose. If efficacy is not achieved with the lowest dose, discontinue use.

2.3 Non-Interchangeability with Other Formulations of Diclofenac

ZORVOLEX capsules are not interchangeable with other formulations of oral diclofenac even if the milligram strength is the same. ZORVOLEX capsules contain diclofenac free acid whereas other diclofenac products contain a salt of diclofenac, i.e., diclofenac potassium or sodium. A 35 mg dose of ZORVOLEX is approximately equal to 37.6 mg of sodium diclofenac or 39.5 mg of potassium diclofenac. Therefore, do not substitute similar dosing strengths of other diclofenac products without taking this into consideration.

3 DOSAGE FORMS AND STRENGTHS

ZORVOLEX (diclofenac) capsules: 18 mg - blue body and light green cap (imprinted IP-203 on the body and 18 mg on the cap in white ink).

ZORVOLEX (diclofenac) capsules: 35 mg - blue body and green cap (imprinted IP-204 on the body and 35 mg on the cap in white ink).

4 CONTRAINDICATIONS

ZORVOLEX is contraindicated in the following patients:

- Known hypersensitivity (e.g., anaphylactic reactions and serious skin reactions) to diclofenac or any components of the drug product [see Warnings and Precautions (5.7, 5.9)]
- History of asthma, urticaria, or other allergic-type reactions after taking aspirin or other NSAIDs. Severe, sometimes fatal, anaphylactic reactions to NSAIDs have been reported in such patients [see Warnings and Precautions (5.7, 5.8)]
- In the setting of coronary artery bypass graft (CABG) surgery [see Warnings and Precautions (5.1)]

5 WARNINGS AND PRECAUTIONS

5.1 Cardiovascular Thrombotic Events

Clinical trials of several COX-2 selective and nonselective NSAIDs of up to three years duration have shown an increased risk of serious cardiovascular (CV) thrombotic events, including myocardial infarction (MI) and stroke, which can be fatal. Based on available data, it is unclear that the risk for CV thrombotic events is similar for all NSAIDs. The relative increase in serious CV thrombotic events over baseline conferred by NSAID use appears to be similar in those with and without known CV disease or risk factors for CV disease. However, patients with known CV disease or risk factors had a higher absolute incidence of excess serious CV thrombotic events, due to their increased baseline rate. Some observational studies found that this increased risk of serious CV thrombotic events began as early as the first weeks of treatment. The increase in CV thrombotic risk has been observed most consistently at higher doses.

To minimize the potential risk for an adverse CV event in NSAID-treated patients, use the lowest effective dose for the shortest duration possible. Physicians and patients should remain alert for the development of such events, throughout the entire treatment course, even in the absence of previous CV symptoms. Patients should be informed about the symptoms of serious CV events and the steps to take if they occur.

There is no consistent evidence that concurrent use of aspirin mitigates the increased risk of serious CV thrombotic events associated with NSAID use. The concurrent use of aspirin and an NSAID, such as diclofenac, increases the risk of serious gastrointestinal (GI) events [see Warnings and Precautions (5.2)].

Status Post Coronary Artery Bypass Graft (CABG) Surgery

Two large, controlled clinical trials of a COX-2 selective NSAID for the treatment of pain in the first 10–14 days following CABG surgery found an increased incidence of myocardial infarction and stroke. NSAIDs are contraindicated in the setting of CABG [see Contraindications (4)].

Post-MI Patients

Observational studies conducted in the Danish National Registry have demonstrated that patients treated with NSAIDs in the post-MI period were at increased risk of reinfarction, CV-related death, and all-cause mortality beginning in the first week of treatment. In this same cohort, the incidence of death in the first year post-MI was 20 per 100 person years in NSAID-treated patients compared to 12 per 100 person years in non-NSAID exposed patients. Although the absolute rate of death declined somewhat after the first year post-MI, the increased relative risk of death in NSAID users persisted over at least the next four years of follow-up.

Avoid the use of ZORVOLEX in patients with a recent MI unless the benefits are expected to outweigh the risk of recurrent CV thrombotic events. If ZORVOLEX is used in patients with a recent MI, monitor patients for signs of cardiac ischemia.

5.2 Gastrointestinal Bleeding, Ulceration, and Perforation

NSAIDs, including diclofenac, cause serious gastrointestinal (GI) adverse events including inflammation, bleeding, ulceration, and perforation of the esophagus, stomach, small intestine, or large intestine, which can be fatal. These serious adverse events can occur at any time, with or without warning symptoms, in patients treated with NSAIDs. Only one in five patients who develop a serious upper GI adverse event on NSAID therapy is symptomatic. Upper GI ulcers, gross bleeding, or perforation caused by NSAIDs occurred in approximately 1% of patients treated for 3-6 months, and in about 2%-4% of patients treated for one year. However, even short-term NSAID therapy is not without risk.

Risk Factors for GI Bleeding, Ulceration, and Perforation

Patients with a prior history of peptic ulcer disease and/or GI bleeding who used NSAIDs had a greater than 10-fold increased risk for developing a GI bleed compared to patients without these risk factors. Other factors that increase the risk of GI bleeding in patients treated with NSAIDs include longer duration of NSAID therapy; concomitant use of oral corticosteroids, aspirin, anticoagulants, or selective serotonin reuptake inhibitors (SSRIs); smoking; use of alcohol; older age; and poor general health status. Most postmarketing reports of fatal GI events occurred in elderly or debilitated patients. Additionally, patients with advanced liver disease and/or coagulopathy are at increased risk for GI bleeding.

Strategies to Minimize the GI Risks in NSAID-treated patients:

- Use the lowest effective dosage for the shortest possible duration.
- Avoid administration of more than one NSAID at a time.
- Avoid use in patients at higher risk unless benefits are expected to outweigh the increased risk of bleeding. For such patients, as well as those with active GI bleeding, consider alternate therapies other than NSAIDs.
- Remain alert for signs and symptoms of GI ulceration and bleeding during NSAID therapy.
- If a serious GI adverse event is suspected, promptly initiate evaluation and treatment, and discontinue ZORVOLEX until a serious GI adverse event is ruled out.
- In the setting of concomitant use of low-dose aspirin for cardiac prophylaxis, monitor patients more closely for evidence of GI bleeding [see Drug Interactions (7)].

5.3 Hepatotoxicity

In clinical trials of diclofenac-containing products, meaningful elevations (i.e., more than 3 times the ULN) of AST (SGOT) were observed in about 2% of approximately 5,700 patients at some time during diclofenac treatment (ALT was not measured in all studies).

In a large, open-label, controlled trial of 3,700 patients treated with oral diclofenac sodium for 2-6 months, patients were monitored first at 8 weeks and 1,200 patients were monitored again at 24 weeks. Meaningful elevations of ALT and/or AST occurred in about 4% of patients and included marked elevations (greater than 8 times the ULN) in about 1% of the 3,700 patients. In that open-label study, a higher incidence of borderline (less than 3 times the ULN), moderate (3-8 times the ULN), and marked (greater than 8 times the ULN) elevations of ALT or AST was observed in patients receiving diclofenac when compared to other NSAIDs. Elevations in transaminases were seen more frequently in patients with osteoarthritis than in those with rheumatoid arthritis.

Almost all meaningful elevations in transaminases were detected before patients became symptomatic. Abnormal tests occurred during the first 2 months of therapy with diclofenac in 42 of the 51 patients in all trials who developed marked transaminase elevations.

In postmarketing reports, cases of drug-induced hepatotoxicity have been reported in the first month, and in some cases, the first 2 months of therapy, but can occur at any time during treatment with diclofenac.

Postmarketing surveillance has reported cases of severe hepatic reactions, including liver necrosis, jaundice, fulminant hepatitis with and without jaundice, and liver failure. Some of these reported cases resulted in fatalities or liver transplantation.

In a European retrospective population-based, case-controlled study, 10 cases of diclofenac associated drug-induced liver injury with current use compared with non-use of diclofenac were associated with a statistically significant 4-fold adjusted odds ratio of liver injury. In this particular study, based on an overall number of 10 cases of liver injury associated with diclofenac, the adjusted odds ratio increased further with female gender, doses of 150 mg or more, and duration of use for more then 90 days.

Physicians should measure transaminases at baseline and periodically in patients receiving long-term therapy with ZORVOLEX, because severe hepatotoxicity may develop without a prodrome of distinguishing symptoms. The optimum times for making the first and subsequent transaminase measurements are not known. Based on clinical trial data and postmarketing experiences, transaminases should be monitored within 4 to 8 weeks after initiating treatment with diclofenac. However, severe hepatic reactions can occur at any time during treatment with diclofenac.

If abnormal liver tests persist or worsen, if clinical signs and/or symptoms consistent with liver disease develop, or if systemic manifestations occur (e.g., eosinophilia, rash, abdominal pain, diarrhea, dark urine, etc.), ZORVOLEX should be discontinued immediately.

Inform patients of the warning signs and symptoms of hepatotoxicity (e.g., nausea, fatigue, lethargy, diarrhea, pruritus, jaundice, right upper quadrant tenderness, and "flu-like" symptoms). If clinical signs and symptoms consistent with liver disease develop, or if systemic manifestations occur (e.g., eosinophilia, rash, etc.), discontinue ZORVOLEX immediately, and perform a clinical evaluation of the patient.

To minimize the potential risk for an adverse liver related event in patients treated with ZORVOLEX, use the lowest effective dose for the shortest duration possible. Exercise caution when prescribing ZORVOLEX with concomitant drugs that are known to be potentially hepatotoxic (e.g., acetaminophen, antibiotics, and anti-epileptics).

5.4 Hypertension

NSAIDs, including ZORVOLEX, can lead to new onset of hypertension or worsening of preexisting hypertension, either of which may contribute to the increased incidence of CV events. Patients taking angiotensin converting enzyme (ACE) inhibitors, thiazide diuretics, or loop diuretics may have impaired response to these therapies when taking NSAIDs [see Drug Interactions (7)].

Monitor blood pressure (BP) during the initiation of NSAID treatment and throughout the course of therapy.

5.5 Heart Failure and Edema

The Coxib and traditional NSAID Trialists' Collaboration meta-analysis of randomized controlled trials demonstrated an approximately two-fold increase in hospitalizations for heart failure in COX-2 selective-treated patients and nonselective NSAID-treated patients compared to placebo-treated patients. In a Danish National Registry study of patients with heart failure, NSAID use increased the risk of MI, hospitalization for heart failure, and death.

Additionally, fluid retention and edema have been observed in some patients treated with NSAIDs. Use of diclofenac may blunt the CV effects of several therapeutic agents used to treat these medical conditions (e.g., diuretics, ACE inhibitors, or angiotensin receptor blockers [ARBs]) [see Drug Interactions (7)].

Avoid the use of ZORVOLEX in patients with severe heart failure unless the benefits are expected to outweigh the risk of worsening heart failure. If ZORVOLEX is used in patients with severe heart failure, monitor patients for signs of worsening heart failure.

5.6 Renal Toxicity and Hyperkalemia

Renal Toxicity

Long-term administration of NSAIDs has resulted in renal papillary necrosis and other renal injury.

Renal toxicity has also been seen in patients in whom renal prostaglandins have a compensatory role in the maintenance of renal perfusion. In these patients, administration of an NSAID may cause a dose-dependent reduction in prostaglandin formation and, secondarily, in renal blood flow, which may precipitate overt renal decompensation. Patients at greatest risk of this reaction are those with impaired renal function, dehydration, hypovolemia, heart failure, liver dysfunction, those taking diuretics and ACE inhibitors or ARBs, and the elderly. Discontinuation of NSAID therapy is usually followed by recovery to the pretreatment state.

No information is available from controlled clinical studies regarding the use of ZORVOLEX in patients with advanced renal disease. The renal effects of ZORVOLEX may hasten the progression of renal dysfunction in patients with preexisting renal disease.

Correct volume status in dehydrated or hypovolemic patients prior to initiating ZORVOLEX. Monitor renal function in patients with renal or hepatic impairment, heart failure, dehydration, or hypovolemia during use of ZORVOLEX [see Drug Interactions (7)]. Avoid the use of ZORVOLEX in patients with advanced renal disease unless the benefits are expected to outweigh the risk of worsening renal function. If ZORVOLEX is used in patients with advanced renal disease, monitor patients for signs of worsening renal function.

Hyperkalemia

Increases in serum potassium concentration, including hyperkalemia, have been reported with use of NSAIDs, even in some patients without renal impairment. In patients with normal renal function, these effects have been attributed to a hyporeninemic-hypoaldosteronism state.

5.7 Anaphylactic Reactions

Diclofenac has been associated with anaphylactic reactions in patients with and without known hypersensitivity to diclofenac and in patients with aspirin-sensitive asthma [see Contraindications (4) and Warnings and Precautions (5.8)].

Seek emergency help if an anaphylactic reaction occurs.

5.8 Exacerbation of Asthma Related to Aspirin Sensitivity

A subpopulation of patients with asthma may have aspirin-sensitive asthma which may include chronic rhinosinusitis complicated by nasal polyps; severe, potentially fatal bronchospasm; and/or intolerance to aspirin and other NSAIDs. Because cross-reactivity between aspirin and other NSAIDs has been reported in such aspirin-sensitive patients, ZORVOLEX is contraindicated in patients with this form of aspirin sensitivity [see Contraindications (4)]. When ZORVOLEX is used in patients with preexisting asthma (without known aspirin sensitivity), monitor patients for changes in the signs and symptoms of asthma.

5.9 Serious Skin Reactions

NSAIDs, including diclofenac, can cause serious skin adverse reactions such as exfoliative dermatitis, Stevens-Johnson Syndrome (SJS), and toxic epidermal necrolysis (TEN), which can be fatal. These serious events may occur without warning. Inform patients about the signs and symptoms of serious skin reactions, and to discontinue the use of ZORVOLEX at the first appearance of skin rash or any other sign of hypersensitivity. ZORVOLEX is contraindicated in patients with previous serious skin reactions to NSAIDs [see Contraindications (4)].

5.10 Premature Closure of Fetal Ductus Arteriosus

Diclofenac may cause premature closure of the fetal ductus arteriosus. Avoid use of NSAIDs, including ZORVOLEX, in pregnant women starting at 30 weeks of gestation (third trimester) [see Use in Specific Populations (8.1)].

5.11 Hematologic Toxicity

Anemia has occurred in NSAID-treated patients. This may be due to occult or gross blood loss, fluid retention, or an incompletely described effect on erythropoiesis. If a patient treated with ZORVOLEX has any signs or symptoms of anemia, monitor hemoglobin or hematocrit.

NSAIDs, including ZORVOLEX, may increase the risk of bleeding events. Co-morbid conditions, such as coagulation disorders, concomitant use of warfarin, other anticoagulants, antiplatelet agents (e.g., aspirin), serotonin reuptake inhibitors (SSRIs) and serotonin norepinephrine reuptake inhibitors (SNRIs) may increase this risk. Monitor these patients for signs of bleeding [see Drug Interactions (7)].

5.12 Masking of Inflammation and Fever

The pharmacological activity of ZORVOLEX in reducing inflammation, and possibly fever, may diminish the utility of diagnostic signs in detecting infections.

5.13 Laboratory Monitoring

Because serious GI bleeding, hepatotoxicity, and renal injury can occur without warning symptoms or signs, consider monitoring patients on long-term NSAID treatment with a CBC and a chemistry profile periodically [see Warnings and Precautions (5.2, 5.3, 5.6)].

6 ADVERSE REACTIONS

The following adverse reactions are discussed in greater detail in other sections of the labeling:

- Cardiovascular Thrombotic Events [see Warnings and Precautions (5.1)]
- GI Bleeding, Ulceration and Perforation [see Warnings and Precautions (5.2)]
- Hepatotoxicity [see Warnings and Precautions (5.3)]
- Hypertension [see Warnings and Precautions (5.4)]
- Heart Failure and Edema [see Warnings and Precautions (5.5)]
- Renal Toxicity and Hyperkalemia [see Warnings and Precautions (5.6)]
- Anaphylactic Reactions [see Warnings and Precautions (5.7)]
- Serious Skin Reactions [see Warnings and Precautions (5.9)]
- Hematologic Toxicity [see Warnings and Precautions (5.11)]

6.1 Clinical Trials Experience

Because clinical trials are conducted under widely varying conditions, adverse reaction rates observed in the clinical trials of a drug cannot be directly compared to rates in the clinical trials of another drug and may not reflect the rates observed in clinical practice.

Adverse Reactions in Patients with Acute Pain

Two-hundred sixteen (216) patients received ZORVOLEX in the completed, 48-hour, double-blind, placebo-controlled, clinical trial of acute pain following bunionectomy. The most frequent adverse reactions in this study are summarized in Table 1.

Table 1 Summary of Adverse Reactions (≥2% in ZORVOLEX 18 mg or 35 mg group) – Phase 3 Study in Patients With Postsurgical Pain
Adverse Reactions | ZORVOLEX 18 mg or 35 mg three times daily [One tablet of hydrocodone/acetaminophen 10 mg/325 mg was permitted every 4 to 6 hours as rescue medication for pain management. There was a greater use of concomitant opioid rescue medication in placebo-treated patients than in ZORVOLEX-treated patients. About 82% of patients in the ZORVOLEX 35 mg group, 85% of the patients in the ZORVOLEX 18 mg group, and 97% of patients in the placebo group took rescue medication for pain management during the study.] N = 216 | Placebo N = 106
Edema | 33% | 32%
Nausea | 27% | 37%
Headache | 13% | 15%
Dizziness | 10% | 16%
Vomiting | 9% | 12%
Constipation | 8% | 4%
Pruritus | 7% | 6%
Flatulence | 3% | 2%
Pain in Extremity | 3% | 1%
Dyspepsia | 2% | 1%

Adverse Reactions in Patients with Osteoarthritis Pain

Two-hundred two (202) patients received ZORVOLEX in the completed, 12-week, double-blind, placebo-controlled, clinical trial of osteoarthritis pain of the knee or hip. The most frequent adverse reactions in this study are summarized in Table 2.

Table 2 Summary of Adverse Reactions (≥2%) – 12-week Phase 3 Study in Patients With Osteoarthritis Pain [Adverse reactions that occurred in ≥2% of patients treated with ZORVOLEX and occurred more frequently than in patients treated with placebo]
Adverse Reactions | ZORVOLEX 35 mg N=202 | Placebo N=103
Nausea | 7% | 2%
Diarrhea | 6% | 3%
Headache | 4% | 3%
Abdominal Pain Upper | 3% | 1%
Sinusitis | 3% | 1%
Vomiting | 3% | 1%
Alanine Aminotransferase Increased | 2% | 0
Blood Creatinine Increased | 2% | 0
Dyspepsia | 2% | 1%
Flatulence | 2% | 0
Hypertension | 2% | 1%

Six-hundred one (601) patients received ZORVOLEX 35 mg either twice or three times daily in a 52-week, open-label, clinical trial in osteoarthritis pain of the knee or hip. Of those, 360 (60%) patients completed the trial. The most frequent adverse reactions in this study are summarized in Table 3.

Table 3 Summary of Adverse Reactions (≥2%) – 52-week Open-label Study in Patients with Osteoarthritis Pain
Adverse Reactions | ZORVOLEX 35 mg N=601
Upper respiratory tract infection | 8%
Headache | 8%
Urinary tract infection | 7%
Diarrhea | 6%
Nasopharyngitis | 6%
Nausea | 6%
Constipation | 5%
Sinusitis | 5%
Osteoarthritis | 5%
Cough | 4%
Alanine aminotransferase increased | 4%
Back pain | 3%
Dyspepsia | 3%
Procedural pain | 3%
Bronchitis | 3%
Hypertension | 3%
Abdominal pain upper | 3%
Influenza | 3%
Arthralgia | 3%
Contusion | 3%
Vomiting | 3%
Abdominal discomfort | 2%
Aspartate aminotransferase increased | 2%
Dizziness | 2%
Fall | 2%
Abdominal pain | 2%

Adverse reactions reported for diclofenac and other NSAIDs:

In patients taking other NSAIDs, the most frequently reported adverse reactions occurring in approximately 1%-10% of patients are:

Gastrointestinal experiences including: abdominal pain, constipation, diarrhea, dyspepsia, flatulence, gross bleeding/perforation, heartburn, nausea, GI ulcers (gastric/duodenal) and vomiting.

Abnormal renal function, anemia, dizziness, edema, elevated liver enzymes, headaches, increased bleeding time, pruritus, rashes and tinnitus.

Additional adverse reactions reported occasionally include:

Body as a Whole: fever, infection, sepsis

Cardiovascular System: congestive heart failure, hypertension, tachycardia, syncope

Digestive System: dry mouth, esophagitis, gastric/peptic ulcers, gastritis, gastrointestinal bleeding, glossitis, hematemesis, hepatitis, jaundice

Hemic and Lymphatic System: ecchymosis, eosinophilia, leukopenia, melena, purpura, rectal bleeding, stomatitis, thrombocytopenia

Metabolic and Nutritional: weight changes

Nervous System: anxiety, asthenia, confusion, depression, dream abnormalities, drowsiness, insomnia, malaise, nervousness, paresthesia, somnolence, tremors, vertigo

Respiratory System: asthma, dyspnea

Skin and Appendages: alopecia, photosensitivity, sweating increased

Special Senses: blurred vision

Urogenital System: cystitis, dysuria, hematuria, interstitial nephritis, oliguria/polyuria, proteinuria, renal failure

Other adverse reactions, which occur rarely are:

Body as a Whole: anaphylactic reactions, appetite changes, death

Cardiovascular System: arrhythmia, hypotension, myocardial infarction, palpitations, vasculitis

Digestive System: colitis, eructation, fulminant hepatitis with and without jaundice, liver failure, liver necrosis, pancreatitis

Hemic and Lymphatic System: agranulocytosis, hemolytic anemia, aplastic anemia, lymphadenopathy, pancytopenia

Metabolic and Nutritional: hyperglycemia

Nervous System: convulsions, coma, hallucinations, meningitis

Respiratory System: respiratory depression, pneumonia

Skin and Appendages: angioedema, toxic epidermal necrolysis, erythema multiforme, exfoliative dermatitis, Stevens-Johnson syndrome, urticaria

Special Senses: conjunctivitis, hearing impairment

7 DRUG INTERACTIONS

See Table 4 for clinically significant drug interactions with diclofenac.

Table 4 Clinically Significant Drug Interactions with Diclofenac
Drugs That Interfere with Hemostasis
Clinical Impact: | - Diclofenac and anticoagulants such as warfarin have a synergistic effect on bleeding. The concomitant use of diclofenac and anticoagulants have an increased risk of serious bleeding compared to the use of either drug alone. - Serotonin release by platelets plays an important role in hemostasis. Case-control and cohort epidemiological studies showed that concomitant use of drugs that interfere with serotonin reuptake and an NSAID may potentiate the risk of bleeding more than an NSAID alone.
Intervention: | Monitor patients with concomitant use of ZORVOLEX with anticoagulants (e.g., warfarin), antiplatelet agents (e.g., aspirin), selective serotonin reuptake inhibitors (SSRIs), and serotonin norepinephrine reuptake inhibitors (SNRIs) for signs of bleeding [see Warnings and Precautions (5.11)].
Aspirin
Clinical Impact: | Controlled clinical studies showed that the concomitant use of NSAIDs and analgesic doses of aspirin does not produce any greater therapeutic effect than the use of NSAIDs alone. In a clinical study, the concomitant use of an NSAID and aspirin was associated with a significantly increased incidence of GI adverse reactions as compared to use of the NSAID alone [see Warnings and Precautions (5.2)].
Intervention: | Concomitant use of ZORVOLEX and analgesic doses of aspirin is not generally recommended because of the increased risk of bleeding [see Warnings and Precautions (5.11)]. ZORVOLEX is not a substitute for low dose aspirin for cardiovascular protection.
ACE Inhibitors, Angiotensin Receptor Blockers, and Beta-Blockers
Clinical Impact: | - NSAIDs may diminish the antihypertensive effect of angiotensin converting enzyme (ACE) inhibitors, angiotensin receptor blockers (ARBs), or beta-blockers (including propranolol). - In patients who are elderly, volume-depleted (including those on diuretic therapy), or have renal impairment, co-administration of an NSAID with ACE inhibitors or ARBs may result in deterioration of renal function, including possible acute renal failure. These effects are usually reversible.
Intervention: | - During concomitant use of ZORVOLEX and ACE-inhibitors, ARBs, or beta-blockers, monitor blood pressure to ensure that the desired blood pressure is obtained. - During concomitant use of ZORVOLEX and ACE-inhibitors or ARBs in patients who are elderly, volume-depleted, or have impaired renal function, monitor for signs of worsening renal function [see Warnings and Precautions (5.6)]. - When these drugs are administered concomitantly, patients should be adequately hydrated. Assess renal function at the beginning of the concomitant treatment and periodically thereafter.
Diuretics
Clinical Impact: | Clinical studies, as well as post-marketing observations, showed that NSAIDs reduced the natriuretic effect of loop diuretics (e.g., furosemide) and thiazide diuretics in some patients. This effect has been attributed to the NSAID inhibition of renal prostaglandin synthesis.
Intervention: | During concomitant use of ZORVOLEX with diuretics, observe patients for signs of worsening renal function, in addition to assuring diuretic efficacy including antihypertensive effects [see Warnings and Precautions (5.6)].
Digoxin
Clinical Impact: | The concomitant use of diclofenac with digoxin has been reported to increase the serum concentration and prolong the half-life of digoxin.
Intervention: | During concomitant use of ZORVOLEX and digoxin, monitor serum digoxin levels.
Lithium
Clinical Impact: | NSAIDs have produced elevations in plasma lithium levels and reductions in renal lithium clearance. The mean minimum lithium concentration increased 15%, and the renal clearance decreased by approximately 20%. This effect has been attributed to NSAID inhibition of renal prostaglandin synthesis.
Intervention: | During concomitant use of ZORVOLEX and lithium, monitor patients for signs of lithium toxicity.
Methotrexate
Clinical Impact: | Concomitant use of NSAIDs and methotrexate may increase the risk for methotrexate toxicity (e.g., neutropenia, thrombocytopenia, renal dysfunction).
Intervention: | During concomitant use of ZORVOLEX and methotrexate, monitor patients for methotrexate toxicity.
Cyclosporine
Clinical Impact: | Concomitant use of ZORVOLEX and cyclosporine may increase cyclosporine's nephrotoxicity.
Intervention: | During concomitant use of ZORVOLEX and cyclosporine, monitor patients for signs of worsening renal function.
NSAIDs and Salicylates
Clinical Impact: | Concomitant use of diclofenac with other NSAIDs or salicylates (e.g., diflunisal, salsalate) increases the risk of GI toxicity, with little or no increase in efficacy [see Warnings and Precautions (5.2)].
Intervention: | The concomitant use of diclofenac with other NSAIDs or salicylates is not recommended.
Pemetrexed
Clinical Impact: | Concomitant use of ZORVOLEX and pemetrexed may increase the risk of pemetrexed-associated myelosuppression, renal, and GI toxicity (see the pemetrexed prescribing information).
Intervention: | During concomitant use of ZORVOLEX and pemetrexed, in patients with renal impairment whose creatinine clearance ranges from 45 to 79 mL/min, monitor for myelosuppression, renal and GI toxicity. NSAIDs with short elimination half-lives (e.g., diclofenac, indomethacin) should be avoided for a period of two days before, the day of, and two days following administration of pemetrexed. In the absence of data regarding potential interaction between pemetrexed and NSAIDs with longer half-lives (e.g., meloxicam, nabumetone), patients taking these NSAIDs should interrupt dosing for at least five days before, the day of, and two days following pemetrexed administration.
Inhibitors or Inducers of Cytochrome P450 2C9
Clinical Impact: | Diclofenac is metabolized by cytochrome P450 enzymes, predominantly by CYP2C9. Co-administration of diclofenac with CYP2C9 inhibitors (e.g. voriconazole) may enhance the exposure and toxicity of diclofenac whereas co-administration with CYP2C9 inducers (e.g. rifampin) may lead to compromised efficacy of diclofenac.
Intervention: | A dosage adjustment may be warranted when diclofenac is administered with CYP2C9 inhibitors or inducers [see Clinical Pharmacology (12.3)].

8 USE IN SPECIFIC POPULATIONS

8.1 Pregnancy

Pregnancy Category C prior to 30 weeks gestation; Category D starting 30 weeks gestation.

Risk Summary

Use of NSAIDs, including ZORVOLEX, during the third trimester of pregnancy increases the risk of premature closure of the fetal ductus arteriosus. Avoid use of NSAIDs, including ZORVOLEX, in pregnant women starting at 30 weeks of gestation (third trimester).

There are no adequate and well-controlled studies of ZORVOLEX in pregnant women.

Data from observational studies regarding potential embryofetal risks of NSAID use in women in the first or second trimesters of pregnancy are inconclusive. In the general U.S. population, all clinically recognized pregnancies, regardless of drug exposure, have a background rate of 2-4% for major malformations, and 15-20% for pregnancy loss.

In animal reproduction studies, no evidence of teratogenicity was observed in mice, rats, and rabbits given diclofenac during the period of organogenesis at doses approximately 1, 1, and 2 times, respectively, the maximum recommended human dose (MRHD) of ZORVOLEX despite the presence of maternal and fetal toxicity at these doses [see Data]. Based on animal data, prostaglandins have been shown to have an important role in endometrial vascular permeability, blastocyst implantation, and decidualization. In animal studies, administration of prostaglandin synthesis inhibitors such as diclofenac, resulted in increased pre- and post-implantation loss.

Clinical Considerations

Labor or Delivery

There are no studies on the effects of ZORVOLEX during labor or delivery. In animal studies, NSAIDs, including diclofenac, inhibit prostaglandin synthesis, cause delayed parturition, and increase the incidence of stillbirth.

Data

Animal data

Reproductive and developmental studies in animals demonstrated that diclofenac sodium administration during organogenesis did not produce teratogenicity despite the induction of maternal toxicity and fetal toxicity in mice at oral doses up to 20 mg/kg/day (approximately equivalent to the maximum recommended human dose [MRHD] of ZORVOLEX, 105 mg/day, based on body surface area (BSA) comparison), and in rats and rabbits at oral doses up to 10 mg/kg/day (approximately 1 and 2 times, respectively, the MRHD based on BSA comparison). In rats, maternally toxic doses were associated with dystocia, prolonged gestation, reduced fetal weights and growth, and reduced fetal survival. Diclofenac has been shown to cross the placental barrier in mice, rats, and humans.

8.2 Lactation

Risk Summary

Based on available data, diclofenac may be present in human milk. The developmental and health benefits of breastfeeding should be considered along with the mother's clinical need for ZORVOLEX and any potential adverse effects on the breastfed infant from the ZORVOLEX or from the underlying maternal condition.

Data

One woman treated orally with a diclofenac salt, 150 mg/day, had a milk diclofenac level of 100 mcg/L, equivalent to an infant dose of about 0.03 mg/kg/day. Diclofenac was not detectable in breast milk in 12 women using diclofenac (after either 100 mg/day orally for 7 days or a single 50 mg intramuscular dose administered in the immediate postpartum period).

8.3 Females and Males of Reproductive Potential

Infertility

Females

Based on the mechanism of action, the use of prostaglandin-mediated NSAIDs, including ZORVOLEX, may delay or prevent rupture of ovarian follicles, which has been associated with reversible infertility in some women. Published animal studies have shown that administration of prostaglandin synthesis inhibitors has the potential to disrupt prostaglandin-mediated follicular rupture required for ovulation. Small studies in women treated with NSAIDs have also shown a reversible delay in ovulation. Consider withdrawal of NSAIDs, including ZORVOLEX, in women who have difficulties conceiving or who are undergoing investigation of infertility.

8.4 Pediatric Use

The safety and effectiveness of ZORVOLEX in pediatric patients has not been established.

8.5 Geriatric Use

Elderly patients, compared to younger patients, are at greater risk for NSAID-associated serious cardiovascular, gastrointestinal, and/or renal adverse reactions. If the anticipated benefit for the elderly patient outweighs these potential risks, start dosing at the low end of the dosing range, and monitor patients for adverse effects [see Warnings and Precautions (5.1, 5.2, 5.3, 5.6, 5.13)].

Diclofenac is known to be substantially excreted by the kidney, and the risk of adverse reactions to this drug may be greater in patients with impaired renal function. Because elderly patients are more likely to have decreased renal function, care should be taken in dose selection, and it may be useful to monitor renal function.

10 OVERDOSAGE

Symptoms following acute NSAID overdosages have been typically limited to lethargy, drowsiness, nausea, vomiting, and epigastric pain, which have been generally reversible with supportive care. Gastrointestinal bleeding has occurred. Hypertension, acute renal failure, respiratory depression, and coma have occurred, but were rare [see Warnings and Precautions (5.1, 5.2, 5.4, 5.6)].

Manage patients with symptomatic and supportive care following an NSAID overdosage. There are no specific antidotes. Consider emesis and/or activated charcoal (60 to 100 grams in adults, 1 to 2 grams per kg of body weight in pediatric patients) and/or osmotic cathartic in symptomatic patients seen within four hours of ingestion or in patients with a large overdosage (5 to 10 times the recommended dosage). Forced diuresis, alkalinization of urine, hemodialysis, or hemoperfusion may not be useful due to high protein binding.

For additional information about overdosage treatment contact a poison control center (1-800-222-1222).

11 DESCRIPTION

ZORVOLEX (diclofenac) capsules are a nonsteroidal anti-inflammatory drug, available as hard gelatin capsules of 18 mg and 35 mg for oral administration. The chemical name is 2-[(2, 6-dichlorophenyl) amino] benzeneacetic acid. The molecular weight is 296.15. Its molecular formula is C14H11Cl2NO2, and it has the following chemical structure.

Diclofenac acid is a white to slight yellowish crystalline powder. Diclofenac acid has a pKa of 4.18 and a logP of 3.03. It is practically insoluble in water and sparingly soluble in ethanol.

The inactive ingredients in ZORVOLEX include a combination of lactose monohydrate, sodium lauryl sulfate, microcrystalline cellulose, croscarmellose sodium and sodium stearyl fumarate. The capsule shells contain gelatin, titanium dioxide, and dyes FD&C blue #1, FD&C blue #2, FDA/E172 Yellow Iron Oxide and FDA/E172 Black Iron Oxide. The imprinting on the gelatin capsules is white edible ink. The 18 mg capsules have a blue body imprinted with IP-203 and light green cap imprinted with 18 mg in white ink. The 35 mg capsules have a blue body imprinted with IP-204 and green cap imprinted with 35 mg in white ink.

12 CLINICAL PHARMACOLOGY

12.1 Mechanism of Action

Diclofenac has analgesic, anti-inflammatory, and antipyretic properties.

The mechanism of action of ZORVOLEX, like that of other NSAIDs, is not completely understood but involves inhibition of cyclooxygenase (COX-1 and COX-2).

Diclofenac is a potent inhibitor of prostaglandin synthesis in vitro. Diclofenac concentrations reached during therapy have produced in vivo effects. Prostaglandins sensitize afferent nerves and potentiate the action of bradykinin in inducing pain in animal models. Prostaglandins are mediators of inflammation. Because diclofenac is an inhibitor of prostaglandin synthesis, its mode of action may be due to a decrease of prostaglandins in peripheral tissues.

12.3 Pharmacokinetics

The relative bioavailability of ZORVOLEX 35 mg capsules was compared to diclofenac potassium immediate-release (IR) tablets 50 mg in 39 healthy subjects under fasted and fed conditions in a single-dose crossover study.

ZORVOLEX 35 mg capsules do not result in an equivalent systemic exposure to 50 mg diclofenac potassium IR tablets.

When taken under fasted conditions, a 20% lower dose of diclofenac in ZORVOLEX capsules resulted in a 23% lower mean systemic exposure (AUCinf) and a 26% lower mean peak concentration (Cmax) compared to diclofenac potassium IR tablets. The time to reach peak concentration (Tmax) was similar for ZORVOLEX and diclofenac potassium IR tablets and was ~1 hour for both.

When taken under fed conditions, a 20% lower dose of diclofenac in ZORVOLEX capsules resulted in a 23% lower mean systemic exposure (AUCinf) and a 48% lower mean Cmax compared to diclofenac potassium IR tablets. The Tmax for ZORVOLEX was delayed by approximately 1 hour compared to diclofenac potassium IR tablets (3.32 hours vs. 2.33 hours, respectively).

When taken under fed conditions, ZORVOLEX capsules resulted in an 11% lower mean systemic exposure (AUCinf) and a 60% lower mean Cmax compared to fasted conditions. Whereas diclofenac potassium IR tablets under fed conditions resulted in 8% - 10% lower mean systemic exposure (AUCinf) and 28% - 43% lower mean Cmax compared to fasted conditions, based on the results from two individual food effect studies. The Tmax for ZORVOLEX was delayed by approximately 2.32 hours under fed conditions compared to fasted conditions (3.32 hours vs. 1.00 hour, respectively), while the Tmax for diclofenac potassium IR tablets was delayed by approximately 1.00 - 1.33 hours under fed conditions compared to fasted conditions (1.70 vs. 0.74 hours and 2.33 vs. 1.00 hours, respectively in two studies).

There were no differences in elimination half-life between ZORVOLEX and diclofenac potassium IR tablets under fasted or fed conditions.

Absorption

Diclofenac is 100% absorbed after oral administration compared to IV administration as measured by urine recovery. However, due to first-pass metabolism, only about 50% of the absorbed dose is systemically available. After repeated oral administration, no accumulation of diclofenac in plasma occurred.

Administration of ZORVOLEX capsules 18 mg and 35 mg was associated with dose proportional pharmacokinetics.

Taking ZORVOLEX with food causes a significant decrease in the rate but not the overall extent of systemic absorption of diclofenac compared with taking ZORVOLEX on an empty stomach. ZORVOLEX capsules results in 60% lower Cmax, 11% lower AUCinf, and 2.32 hours delayed Tmax (1.0 hour during fasted versus 3.32 hours during fed) under the fed condition compared to the fasted condition. The effectiveness of ZORVOLEX when taken with food has not been studied in clinical studies. The decreased Cmax may be associated with decreased effectiveness. Taking ZORVOLEX with food may cause a reduction in effectiveness compared to taking ZORVOLEX on an empty stomach.

Distribution

The apparent volume of distribution (V/F) of diclofenac potassium is 1.3 L/kg. Diclofenac is more than 99% bound to human serum proteins, primarily to albumin. Serum protein binding is constant over the concentration range (0.15-105 mg/mL) achieved with recommended doses.

Diclofenac diffuses into and out of the synovial fluid. Diffusion into the joint occurs when plasma levels are higher than those in the synovial fluid, after which the process reverses and synovial fluid levels are higher than plasma levels. It is not known whether diffusion into the joint plays a role in the effectiveness of diclofenac.

Elimination

Diclofenac is eliminated through metabolism and subsequent urinary and biliary excretion of the glucuronide and the sulfate conjugates of the metabolites. The terminal half-life of unchanged diclofenac is approximately 2 hours.

Metabolism

Five diclofenac metabolites have been identified in human plasma and urine. The metabolites include 4'-hydroxy-, 5-hydroxy-, 3'-hydroxy-, 4',5-dihydroxy- and 3'-hydroxy-4'-methoxy diclofenac. The major diclofenac metabolite, 4'-hydroxy-diclofenac, has very weak pharmacologic activity. The formation of 4'-hydroxy-diclofenac is primarily mediated by CYP2C9. Both diclofenac and its oxidative metabolites undergo glucuronidation or sulfation followed by biliary excretion. Acylglucuronidation mediated by UGT2B7 and oxidation mediated by CYP2C8 may also play a role in diclofenac metabolism. CYP3A4 is responsible for the formation of minor metabolites, 5-hydroxy and 3'-hydroxy-diclofenac. In patients with renal dysfunction, peak concentrations of metabolites 4'-hydroxy and 5-hydroxy-diclofenac were approximately 50% and 4% of the parent compound after single oral dosing compared to 27% and 1% in normal healthy subjects.

Excretion

Diclofenac is eliminated through metabolism and subsequent urinary and biliary excretion of the glucuronide and the sulfate conjugates of the metabolites. Little or no free unchanged diclofenac is excreted in the urine. Approximately 65% of the dose is excreted in the urine, and approximately 35% in the bile as conjugates of unchanged diclofenac plus metabolites. Because renal elimination is not a significant pathway of elimination for unchanged diclofenac, dosing adjustment in patients with mild to moderate renal dysfunction is not necessary. The terminal half-life of unchanged diclofenac is approximately 2 hours.

Specific Populations

Pediatric: The pharmacokinetics of ZORVOLEX has not been investigated in pediatric patients.

Race: Pharmacokinetic differences due to race/ethnicity have not been identified.

Hepatic Impairment: No dedicated diclofenac pharmacokinetics studies in patients with hepatic impairment were conducted. Hepatic metabolism accounts for almost 100% of diclofenac elimination. Therefore, in patients with hepatic impairment, start with the lowest dose and if efficacy is not achieved, consider use of an alternate product [see Warnings and Precautions (5.3)].

Renal Impairment: Diclofenac pharmacokinetics has been investigated in subjects with renal insufficiency. No differences in the pharmacokinetics of diclofenac have been detected in studies of patients with renal impairment. In patients with renal impairment (inulin clearance 60-90, 30-60, and less than 30 mL/min; N=6 in each group), AUC values and elimination rate were comparable to those in healthy subjects [see Warnings and Precautions (5.6)].

Drug Interaction Studies

Aspirin: When NSAIDs were administered with aspirin, the protein binding of NSAIDs were reduced, although the clearance of free NSAID was not altered. The clinical significance of this interaction is not known. See Table 4 for clinically significant drug interactions of NSAIDs with aspirin [see Drug Interactions (7)].

13 NONCLINICAL TOXICOLOGY

13.1 Carcinogenesis, Mutagenesis, and Impairment of Fertility

Carcinogenesis

Long-term carcinogenicity studies in rats given diclofenac sodium up to 2 mg/kg/day (approximately 0.2 times the maximum recommended human dose [MRHD] of ZORVOLEX based on body surface area [BSA] comparison) have revealed no significant increase in tumor incidence. A 2-year carcinogenicity study conducted in mice employing diclofenac sodium at doses up to 0.3 mg/kg/day (approximately 0.014 times the MRHD based on BSA comparison) in males and 1 mg/kg/day (approximately 0.04 times the MRHD based on BSA comparison) in females did not reveal any oncogenic potential.

Mutagenesis

Diclofenac sodium did not show mutagenic activity in in vitro point mutation assays in mammalian (mouse lymphoma) and microbial (yeast, Ames) test systems and was nonmutagenic in several mammalian in vitro and in vivo tests, including dominant lethal and male germinal epithelial chromosomal aberration studies in Chinese hamsters.

Impairment of Fertility

Diclofenac sodium administered to male and female rats at 4 mg/kg/day (approximately 0.4 times the MRHD based on BSA comparison) did not affect fertility.

14 CLINICAL STUDIES

Acute Pain

The efficacy of ZORVOLEX in the management of acute pain was demonstrated in a single multicenter, randomized, double-blind, placebo-controlled, parallel arm study comparing ZORVOLEX 18 mg and 35 mg taken three times a day, placebo, and celecoxib in patients with pain following bunionectomy. The study enrolled 428 patients with a mean age of 40 years (range 18 to 65 years) and a minimum pain intensity rating of at least 40 mm on a 100-mm visual analog scale (VAS) during the 9-hour period after discontinuation of the anesthetic block following bunionectomy surgery. Patients were randomized equally across the treatment groups.

The mean and range (in parenthesis) of pain intensities on the VAS at baseline were 74 mm (44 to 100 mm), 77 mm (41 to 100 mm), and 76 mm (40 to 100 mm) for the ZORVOLEX 35 mg, ZORVOLEX 18 mg, and placebo groups, respectively. One tablet of hydrocodone/acetaminophen 10 mg/325 mg was permitted every 4 to 6 hours as rescue medication. About 82% of patients in the ZORVOLEX 35 mg group, 85% of the patients in the ZORVOLEX 18 mg group, and 97% of patients in the placebo group took rescue medication for pain management during the study.

The average pain intensities over time are depicted for the treatment groups in Figure 1. Both ZORVOLEX 18 mg and 35 mg demonstrated efficacy in pain intensity reduction compared with placebo, as measured by the sum of pain intensity difference over 0 to 48 hours after the first dose.

Figure 1 Average Pain Intensity Over 48 Hours for ZORVOLEX 18 mg, ZORVOLEX 35 mg, and Placebo Groups

Osteoarthritis Pain

The efficacy of ZORVOLEX in the management of osteoarthritis pain was demonstrated in a single multicenter, randomized, double-blind, placebo-controlled, parallel-arm study comparing ZORVOLEX 35 mg taken twice a day or three times a day and placebo in patients with osteoarthritis of the knee or hip. The study enrolled 305 patients with a mean age of 62 (range 41 to 90 years). Osteoarthritis pain was measured using the Western Ontario and McMaster University Osteoarthritis Index Pain Subscale (WOMAC Pain Subscale). Mean baseline WOMAC Pain Subscale Score across treatment groups was 75 mm using a 0 to 100 mm visual analog scale.

The primary efficacy parameter was the change from baseline at 12 weeks in the WOMAC Pain Subscale. ZORVOLEX 35 mg three times a day reduced osteoarthritis pain compared with placebo, as measured by WOMAC Pain Subscale Score. The distribution (%) of patients achieving various percentage reductions in pain intensity at Week 12 are depicted in Figure 2.

Figure 2 Distribution (%) of Patients Achieving Various Percentage Reductions in Pain Intensity at Week 12

16 HOW SUPPLIED/STORAGE AND HANDLING

ZORVOLEX (diclofenac) capsules are supplied as:

- 18 mg - blue body and light green cap (imprinted IP-203 on the body and 18 mg on the cap in white ink)
  - NDC (42211-203-23), Bottles of 30 capsules
  - NDC (42211-203-29), Bottles of 90 capsules
- 35 mg - blue body and green cap (imprinted IP-204 on the body and 35 mg on the cap in white ink)
  - NDC (42211-204-23), Bottles of 30 capsules
  - NDC (42211-204-29), Bottles of 90 capsules

Storage

Store at room temperature 20°C to 25°C (68°F to 77°F); excursions permitted between 15°C to 30°C (59°F to 86°F) [see USP Controlled Room Temperature].

Store in the original container and keep the bottle tightly closed to protect from moisture. Dispense in a tight container if package is subdivided.

17 PATIENT COUNSELING INFORMATION

Advise the patient to read the FDA-approved patient labeling (Medication Guide) that accompanies each prescription dispensed. Inform patients, families, or their caregivers of the following information before initiating therapy with ZORVOLEX and periodically during the course of ongoing therapy.

Cardiovascular Thrombotic Events

Advise patients to be alert for the symptoms of cardiovascular thrombotic events, including chest pain, shortness of breath, weakness, or slurring of speech, and to report any of these symptoms to their health care provider immediately [see Warnings and Precautions (5.1)].

Gastrointestinal Bleeding, Ulceration, and Perforation

Advise patients to report symptoms of ulcerations and bleeding, including epigastric pain, dyspepsia, melena, and hematemesis to their health care provider. In the setting of concomitant use of low-dose aspirin for cardiac prophylaxis, inform patients of the increased risk for and the signs and symptoms of GI bleeding [see Warnings and Precautions (5.2)].

Hepatotoxicity

Inform patients of the warning signs and symptoms of hepatotoxicity (e.g., nausea, fatigue, lethargy, pruritus, diarrhea, jaundice, right upper quadrant tenderness, and "flu-like" symptoms). If these occur, instruct patients to stop ZORVOLEX and seek immediate medical therapy [see Warnings and Precautions (5.3)].

Heart Failure and Edema

Advise patients to be alert for the symptoms of congestive heart failure including shortness of breath, unexplained weight gain, or edema and to contact their healthcare provider if such symptoms occur [see Warnings and Precautions (5.5)].

Anaphylactic Reactions

Inform patients of the signs of an anaphylactic reaction (e.g., difficulty breathing, swelling of the face or throat). Instruct patients to seek immediate emergency help if these occur [see Contraindications (4) and Warnings and Precautions (5.7)].

Serious Skin Reactions

Advise patients to stop ZORVOLEX immediately if they develop any type of rash and to contact their healthcare provider as soon as possible [see Warnings and Precautions (5.9)].

Female Fertility

Advise females of reproductive potential who desire pregnancy that NSAIDs, including ZORVOLEX, may be associated with a reversible delay in ovulation [see Use in Specific Populations (8.3)].

Fetal Toxicity

Inform pregnant women to avoid use of ZORVOLEX and other NSAIDs starting at 30 weeks gestation because of the risk of the premature closing of the fetal ductus arteriosus [see Warnings and Precautions (5.10) and Use in Specific Populations (8.1)].

Avoid Concomitant Use of NSAIDs

Inform patients that the concomitant use of ZORVOLEX with other NSAIDs or salicylates (e.g., diflunisal, salsalate) is not recommended due to the increased risk of gastrointestinal toxicity, and little or no increase in efficacy [see Warnings and Precautions (5.2) and Drug Interactions (7)]. Alert patients that NSAIDs may be present in "over the counter" medications for treatment of colds, fever, or insomnia.

Use of NSAIDs and Low-Dose Aspirin

Inform patients not to use low-dose aspirin concomitantly with ZORVOLEX until they talk to their healthcare provider [see Drug Interactions (7)].

Manufactured (under license from iCeutica Pty Ltd.) for and Distributed by:
Iroko Pharmaceuticals, LLC
Philadelphia, PA 19112

Issued: May/2016

Medication Guide for Nonsteroidal Anti-inflammatory Drugs (NSAIDs)

What is the most important information I should know about medicines called Nonsteroidal Anti-inflammatory Drugs (NSAIDs)?
NSAIDs can cause serious side effects, including:

- Increased risk of a heart attack or stroke that can lead to death. This risk may happen early in treatment and may increase:
  - with increasing doses of NSAIDs
  - with longer use of NSAIDs
  Do not take NSAIDs right before or after a heart surgery called a "coronary artery bypass graft (CABG)."
  Avoid taking NSAIDs after a recent heart attack, unless your healthcare provider tells you to. You may have an increased risk of another heart attack if you take NSAIDs after a recent heart attack.
- Increased risk of bleeding, ulcers, and tears (perforation) of the esophagus (tube leading from the mouth to the stomach), stomach and intestines:
  - anytime during use
  - without warning symptoms
  - that may cause death
  The risk of getting an ulcer or bleeding increases with:
  - past history of stomach ulcers, or stomach or intestinal bleeding with use of NSAIDs
  - taking medicines called "corticosteroids", "anticoagulants", "SSRIs", or "SNRIs"

- increasing doses of NSAIDs
- longer use of NSAIDs
- smoking
- drinking alcohol

- older age
- poor health
- advanced liver disease
- bleeding problems

NSAIDs should only be used:

- exactly as prescribed
- at the lowest dose possible for your treatment
- for the shortest time needed

What are NSAIDs?

NSAIDs are used to treat pain and redness, swelling, and heat (inflammation) from medical conditions such as different types of arthritis, menstrual cramps, and other types of short-term pain.

Who should not take NSAIDs?
Do not take NSAIDs:

- if you have had an asthma attack, hives, or other allergic reaction with aspirin or any other NSAIDs.
- right before or after heart bypass surgery.

Before taking NSAIDs, tell your healthcare provider about all of your medical conditions, including if you:

- have liver or kidney problems
- have high blood pressure
- have asthma
- are pregnant or plan to become pregnant. Talk to your healthcare provider if you are considering taking NSAIDs during pregnancy. You should not take NSAIDs after 29 weeks of pregnancy.
- are breastfeeding or plan to breast feed.

Tell your healthcare provider about all of the medicines you take, including prescription or over-the-counter medicines, vitamins or herbal supplements. NSAIDs and some other medicines can interact with each other and cause serious side effects. Do not start taking any new medicine without talking to your healthcare provider first.

What are the possible side effects of NSAIDs?
NSAIDs can cause serious side effects, including:
See "What is the most important information I should know about medicines called Nonsteroidal Anti-inflammatory Drugs (NSAIDs)?"

- new or worse high blood pressure
- heart failure
- liver problems including liver failure
- kidney problems including kidney failure
- low red blood cells (anemia)
- life-threatening skin reactions
- life-threatening allergic reactions
- Other side effects of NSAIDs include: stomach pain, constipation, diarrhea, gas, heartburn, nausea, vomiting, and dizziness.

Get emergency help right away if you get any of the following symptoms:

- shortness of breath or trouble breathing
- chest pain
- weakness in one part or side of your body

- slurred speech
- swelling of the face or throat

Stop taking your NSAID and call your healthcare provider right away if you get any of the following symptoms:

- nausea
- more tired or weaker than usual
- diarrhea
- itching
- your skin or eyes look yellow
- indigestion or stomach pain
- flu-like symptoms

- vomit blood
- there is blood in your bowel movement or it is black and sticky like tar
- unusual weight gain
- skin rash or blisters with fever
- swelling of the arms, legs, hands and feet

If you take too much of your NSAID, call your healthcare provider or get medical help right away.

These are not all the possible side effects of NSAIDs. For more information, ask your healthcare provider or pharmacist about NSAIDs.

Call your doctor for medical advice about side effects. You may report side effects to FDA at 1-800-FDA-1088.

Other information about NSAIDs

- Aspirin is an NSAID but it does not increase the chance of a heart attack. Aspirin can cause bleeding in the brain, stomach, and intestines. Aspirin can also cause ulcers in the stomach and intestines.
- Some NSAIDs are sold in lower doses without a prescription (over-the-counter). Talk to your healthcare provider before using over-the-counter NSAIDs for more than 10 days.

General information about the safe and effective use of NSAIDs

Medicines are sometimes prescribed for purposes other than those listed in a Medication Guide. Do not use NSAIDs for a condition for which it was not prescribed. Do not give NSAIDs to other people, even if they have the same symptoms that you have. It may harm them.

If you would like more information about NSAIDs, talk with your healthcare provider. You can ask your pharmacist or healthcare provider for information about NSAIDs that is written for health professionals.

Manufactured (under license from iCeutica Pty Ltd) for and Distributed by:
Iroko Pharmaceuticals, LLC
One Kew Place
150 Rouse Boulevard
Philadelphia, PA 19112
For more information, go to www.iroko.com or call 1-877-757-0676.

This Medication Guide has been approved by the U.S. Food and Drug Administration.

Issued or Revised: May 2016

PRINCIPAL DISPLAY PANEL - 18 mg Capsule Bottle Label

N 42211-203-29

Zorvolex™
(diclofenac) capsules

18 mg
per capsule

Rx Only
90 Capsules

Distributed by IROKO®

PRINCIPAL DISPLAY PANEL - 35 mg Capsule Bottle Label

N 42211-204-29

Zorvolex™
(diclofenac) capsules

35 mg
per capsule

Rx Only
90 Capsules

Distributed by IROKO®